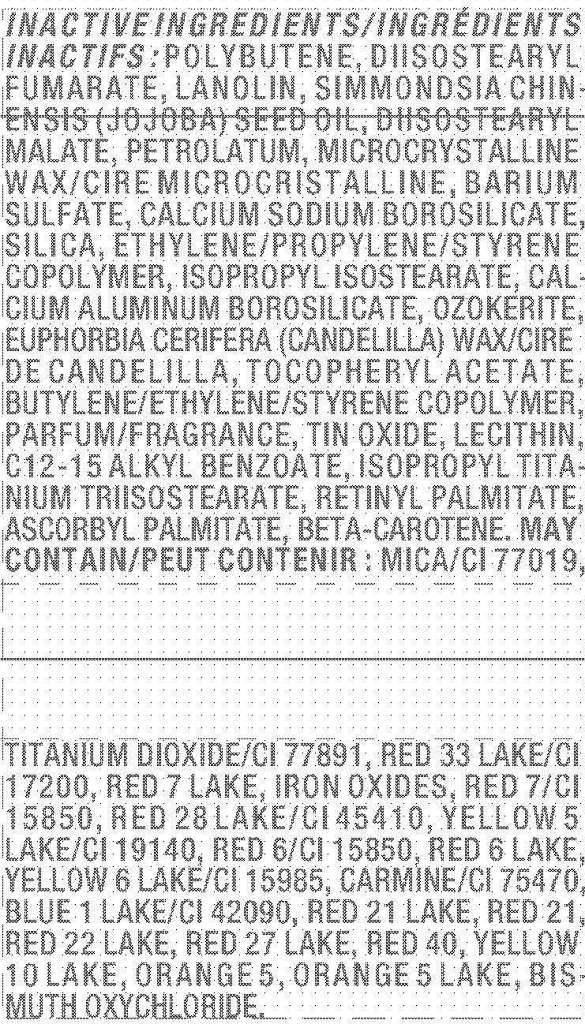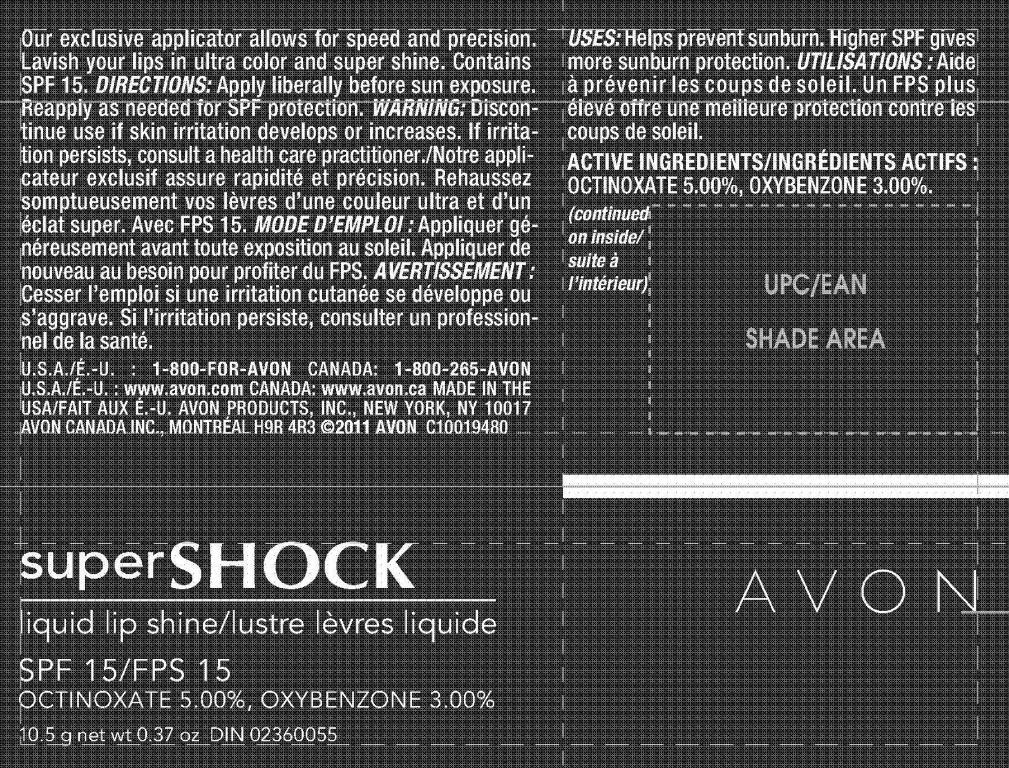 DRUG LABEL: superSHOCK
NDC: 10096-0258 | Form: LIPSTICK
Manufacturer: Avon Products, Inc.
Category: otc | Type: HUMAN OTC DRUG LABEL
Date: 20110419

ACTIVE INGREDIENTS: OCTINOXATE	 0.525 g/10.5 g; OXYBENZONE	 0.315 g/10.5 g

DOSAGE AND ADMINISTRATION

DIRECTIONS: Apply liberally before sun exposure.
Reapply as needed for SPF protection.

WARNINGS

WARNING: Discontinue
use if skin irritation develops or increases. If irritation
persists, consult a health care practitioner.

INDICATIONS AND USAGE

USES: Helps prevent sunburn. Higher SPF gives
more sunburn protection.

ACTIVE INGREDIENTS/INGRÉDIENTS ACTIFS :
OCTINOXATE 5.00%, OXYBENZONE 3.00%.

INACTIVE INGREDIENTS/ INGRÉDIENTS
INACTIFS : POLYBUTENE, DIISOSTEARYL
FUMARATE, LANOLIN, SIMMONDSIA CHINENSIS
(JOJOBA) SEED OIL, DIISOSTEARYL
MALATE, PETROLATUM, MICROCRYSTALLINE
WAX/CIRE MICROCRISTALLINE, BARIUM
SULFATE, CALCIUM SODIUM BOROSILICATE,
SILICA, ETHYLENE/PROPYLENE/STYRENE
COPOLYMER, ISOPROPYL ISOSTEARATE, CALCIUM
ALUMINUM BOROSILICATE, OZOKERITE,
EUPHORBIA CERIFERA (CANDELILLA) WAX/CIRE
DE CANDELILLA, TOCOPHERYL ACETATE,
BUTYLENE/ETHYLENE/STYRENE COPOLYMER,
PARFUM/FRAGRANCE, TIN OXIDE, LECITHIN,
C12-15 ALKYL BENZOATE, ISOPROPYL TITANIUM
TRIISOSTEARATE, RETINYL PALMITATE,
ASCORBYL PALMITATE, BETA-CAROTENE. MAY
CONTAIN/PEUT CONTENIR : MICA/CI 77019,
TITANIUM DIOXIDE/CI 77891, RED 33 LAKE/CI
17200, RED 7 LAKE, IRON OXIDES, RED 7/CI
15850, RED 28 LAKE/CI 45410, YELLOW 5
LAKE/CI 19140, RED 6/CI 15850, RED 6 LAKE,
YELLOW 6 LAKE/CI 15985, CARMINE/CI 75470,
BLUE 1 LAKE/CI 42090, RED 21 LAKE, RED 21,
RED 22 LAKE, RED 27 LAKE, RED 40, YELLOW
10 LAKE, ORANGE 5, ORANGE 5 LAKE, BISMUTH
OXYCHLORIDE.